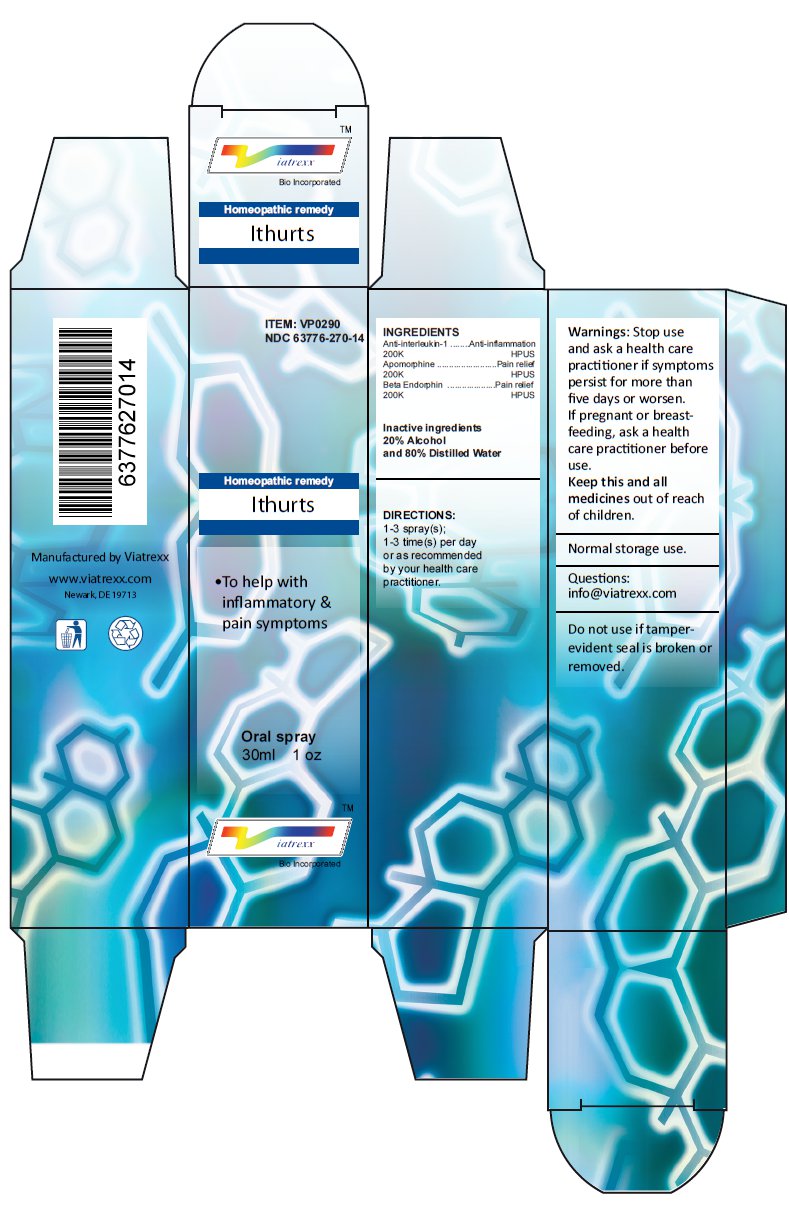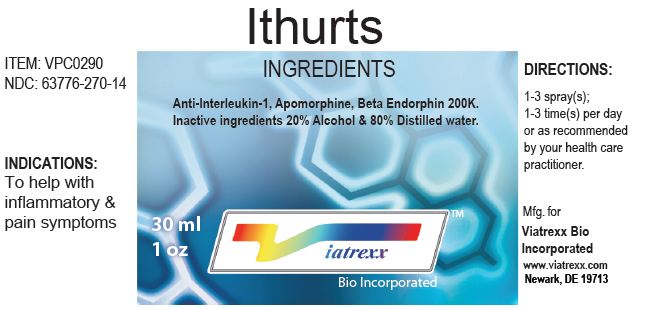 DRUG LABEL: Ithurts
NDC: 63776-270 | Form: SPRAY
Manufacturer: VIATREXX BIO INCORPORATED
Category: homeopathic | Type: HUMAN OTC DRUG LABEL
Date: 20221130

ACTIVE INGREDIENTS: ANTI-INTERLEUKIN-1.ALPHA. IMMUNOGLOBULIN G RABBIT 200 [kp_C]/1 mL; APOMORPHINE 200 [kp_C]/1 mL; METENKEFALIN 200 [kp_C]/1 mL
INACTIVE INGREDIENTS: ALCOHOL; WATER

Ithurts

Active Ingredients

Anti-interleukin-1 200K, Apomorphine 200K, Beta Endorphin 200K

Purpose

Anti-Interleukin-1 | Anti-inflammation
Apomorphine | Pain relief
Beta endorphin | Pain relief

Uses

To help with inflammatory & pain symptoms

Warnings

Stop use and ask a health care practitioner if symptoms persist for more than five days or worsen. If pregnant or breastfeeding, ask a health care practitioner before use.

KEEP OUT OF REACH OF CHILDREN

Keep this and all medicines out of reach of children.

Directions

1-3 spray(s); 1-3 time(s) per day or as recommended by your health care practitioner.

Other Ingredients

Alcohol and Water

Other Information

Normal storage use.
Do not use if tamper-evident seal is broken or removed.

Principal Display Panel

ITEM: VPC0290
NDC 63776-270-14
Homeopathic remedy
Ithurts
• To help with inflammatory & pain symptoms
Oral spray
30ml 1 oz
Viatrexx™ Bio Incorporated
Manufactured by Viatrexx
www.viatrexx.com
Newark, DE 19713

Ithurts
30 mL
1 oz
Viatrexx™ Bio Incorporated
ITEM: VPC0290
NDC: 63776-270-14
INDICATIONS:
To help with inflammatory & pain symptoms
DIRECTIONS:
1-3 spray(s); 1-3 time(s) per day or as recommended by your health care practitioner.
Mfg. for
Viatrexx Bio Incorporated
www.viatrexx.com
Newark, DE 19713